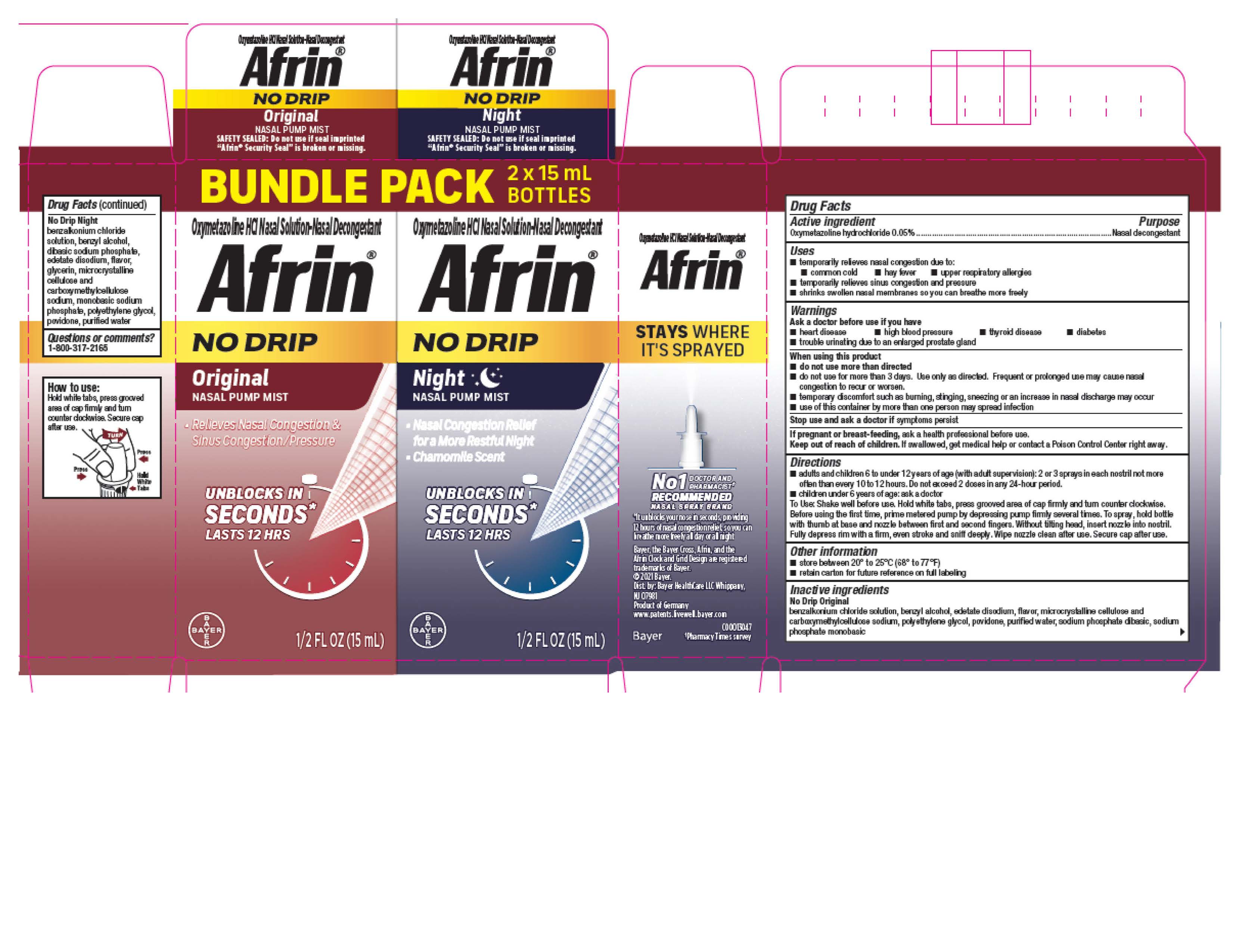 DRUG LABEL: Afrin No Drip
NDC: 11523-0147 | Form: KIT | Route: NASAL
Manufacturer: Bayer HealthCare LLC.
Category: otc | Type: HUMAN OTC DRUG LABEL
Date: 20251204

ACTIVE INGREDIENTS: OXYMETAZOLINE HYDROCHLORIDE 0.05 g/100 mL; OXYMETAZOLINE HYDROCHLORIDE 0.5 mg/1 mL
INACTIVE INGREDIENTS: POLYETHYLENE GLYCOL, UNSPECIFIED; CARBOXYMETHYLCELLULOSE SODIUM; WATER; SODIUM PHOSPHATE, MONOBASIC; EDETATE DISODIUM; CELLULOSE, MICROCRYSTALLINE; BENZYL ALCOHOL; POVIDONE; SODIUM PHOSPHATE, DIBASIC; BENZALKONIUM CHLORIDE; POLYETHYLENE GLYCOL, UNSPECIFIED; WATER; SODIUM PHOSPHATE, MONOBASIC; EDETATE DISODIUM; CELLULOSE, MICROCRYSTALLINE; BENZYL ALCOHOL; POVIDONE; SODIUM PHOSPHATE, DIBASIC; BENZALKONIUM CHLORIDE; CARBOXYMETHYLCELLULOSE SODIUM

Afrin® No Drip Original/Night Pump Mist Bundle Pack

Drug Facts

Active ingredient

Oxymetazoline hydrochloride 0.05%

Purpose

Nasal decongestant

Uses

- temporarily relieves nasal congestion due to:
  - common cold
  - hay fever
  - upper respiratory allergies
- temporarily relieves sinus congestion and pressure
- shrinks swollen nasal membranes so you can breathe more freely

Warnings

Ask a doctor before use if you have

- heart disease
- high blood pressure
- thyroid disease
- diabetes
- trouble urinating due to an enlarged prostate gland

When using this product

- do not use more than directed
- do not use for more than 3 days. Use only as directed. Frequent or prolonged use may cause nasal congestion to recur or worsen.
- temporary discomfort such as burning, stinging, sneezing or an increase in nasal discharge may occur
- use of this container by more than one person may spread infection

Stop use and ask a doctor if symptoms persist

PREGNANCY OR BREAST FEEDING

If pregnant or breast-feeding, ask a health professional before use.

Keep out of reach of children. If swallowed, get medical help or contact a Poison Control Center right away.

Directions

- adults and children 6 to under 12 years of age (with adult supervision): 2 or 3 sprays in each nostril not more often than every 10 to 12 hours. Do not exceed 2 doses in any 24-hour period.
- children under 6 years of age: ask a doctor.

To Use: Shake well before use. Hold white tabs, press grooved area of cap firmly and turn counter clockwise. Before using the first time, prime metered pump by depressing pump firmly several times. To spray, hold bottle with thumb at base and nozzle between first and second fingers. Without tilting head, insert nozzle into nostril. Fully depress rim with a firm, even stroke and sniff deeply. Wipe nozzle clean after use.

Other information

- store between 20° to 25°C (68° to 77°F)
- retain carton for future reference on full labeling

Inactive ingredients

No Drip Original

benzalkonium chloride solution, benzyl alcohol, edetate disodium, flavor, microcrystalline cellulose and carboxymethylcellulose sodium, polyethylene glycol, povidone, purified water, sodium phosphate dibasic, sodium phosphate monobasic

No Drip Night

benzalkonium chloride solution, benzyl alcohol, dibasic sodium phosphate, edetate disodium, flavor, glycerin, microcrystalline cellulose and carboxymethylcellulose sodium, monobasic sodium phosphate, polyethylene glycol, povidone, purified water

Questions or comments? 1-800-317-2165

PRINCIPAL DISPLAY PANEL - Bundle Pack Carton

BUNDLE PACK 2 X 15 mL Bottles

Oxymetazoline HCl Nasal Solution-Nasal Decongestant

Afrin®
No Drip

Original

NASAL PUMP MIST

- Relieves Nasal Congestion & Sinus Congestion/Pressure

Unblocks in

SECONDS*

Lasts 12 HRS

1/2 FL OZ (15 mL)

Oxymetazoline HCl Nasal Solution-Nasal Decongestant

Afrin ®
No Drip

Night

NASAL PUMP MIST

- Nasal Congestion Relief for a More Restful Night
- Chamomile Scent

Unblocks in

SECONDS*

Lasts 12 HRS

1/2 FL OZ (15 mL)